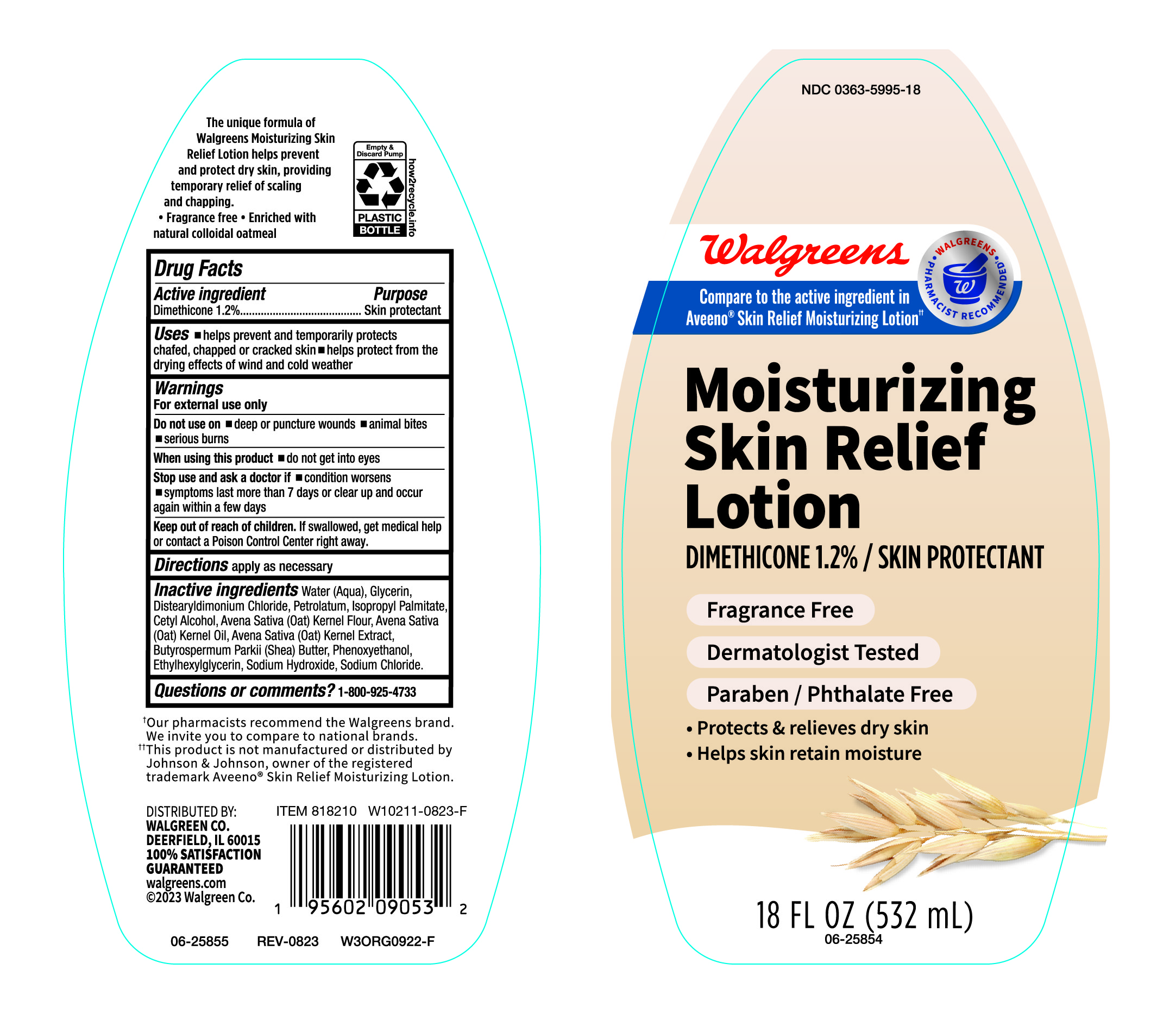 DRUG LABEL: Skin Relief
NDC: 0363-5995 | Form: LOTION
Manufacturer: Walgreen
Category: otc | Type: HUMAN OTC DRUG LABEL
Date: 20240614

ACTIVE INGREDIENTS: DIMETHICONE 1200 mg/100 mL
INACTIVE INGREDIENTS: PHENOXYETHANOL; SHEA BUTTER; SODIUM CHLORIDE; OAT KERNEL OIL; OATMEAL; PETROLATUM; WATER; CETYL ALCOHOL; ETHYLHEXYLGLYCERIN; GLYCERIN; ISOPROPYL PALMITATE; OAT; DISTEARYLDIMONIUM CHLORIDE; SODIUM HYDROXIDE

Moisturizing Skin Relief Lotion, NDC-0363-5995

Active Ingredient

Dimethicone 1.2%

Purpose

Skin protectant

Uses

- Helps prevent and temporarily protects chafed, chapped or cracked skin.
- Helps protect from the drying effects of wind and cold weather.

Warnings

For External use only

Do not use on

- Deep or puncture wounds
- animal bites.
- Serious burns.

When using this product

- do not get into eyes

Stop use and ask a doctor if

- Condition worsens
- Symptoms last more than 7 days or clear up and occur again within a few days.

Keep out of reach of children

If swallowed, get medical help or contact a Poison Control Center right away.

Directions

Apply as necessary

Inactive Ingredients

Water (Aqua), Glycerin, Distearyldimonium Chloride, Petrolatum, Isopropyl Palmitate, Cetyl Alcohol, Avena Sativa (Oat) Kernel Flour, Avena Sativa (Oat) Kernel Oil, Avena Sativa (Oat) Kernel Extract, Butyrospermum Parkii (Shea) Butter, Phenoxyethanol, Ethylhexylglycerin, Sodium Hydroxide, Sodium Chloride.

Questions or Comments?

1-800-925-4733